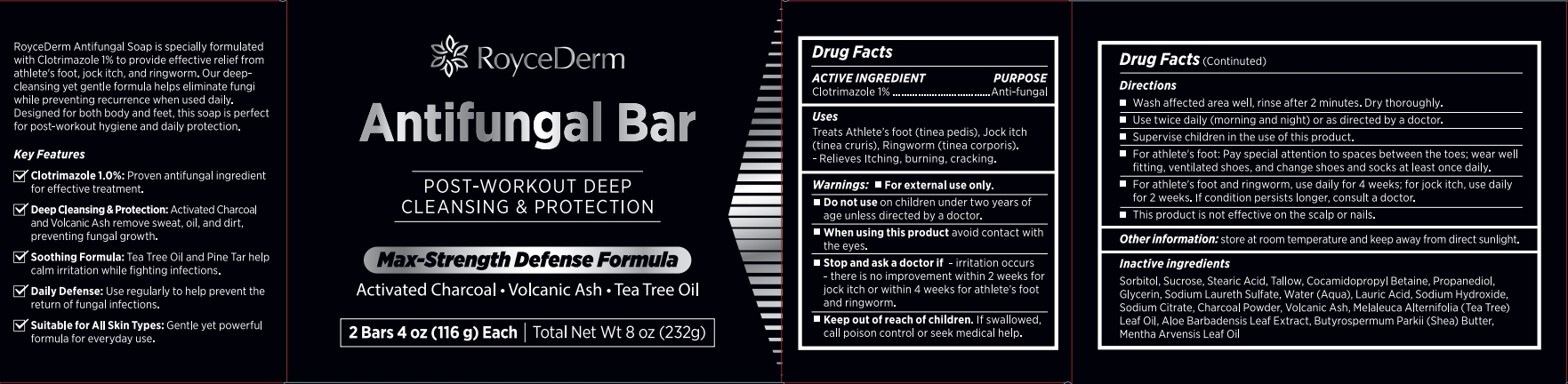 DRUG LABEL: RoyceDerm Antifungal Bar
NDC: 85424-005 | Form: SOAP
Manufacturer: RoyceDerm LLC
Category: otc | Type: HUMAN OTC DRUG LABEL
Date: 20250725

ACTIVE INGREDIENTS: CLOTRIMAZOLE 2.32 g/232 g
INACTIVE INGREDIENTS: BUTYROSPERMUM PARKII (SHEA) BUTTER; SORBITOL; STEARIC ACID; TALLOW; GLYCERIN; PROPANEDIOL; SUCROSE; COCAMIDOPROPYL BETAINE; SODIUM HYDROXIDE; MENTHA ARVENSIS LEAF OIL; SODIUM CITRATE; ALOE BARBADENSIS LEAF JUICE; SODIUM LAURETH SULFATE; AQUA; CHARCOAL POWDER; MELALEUCA ALTERNIFOLIA (TEA TREE) LEAF OIL; LAURIC ACID

Initial Drug Listing - RoyceDerm Antifungal Bar

ACTIVE INGREDIENT

Clotrimazole 1%

PURPOSE

Anti-fungal

DOSAGE AND ADMINISTRATION

Treats Athlete's foot (tinea pedis), Jock itch(tinea cruris),Ringworm (tinea corporis).-Relieves ltching, burning, cracking.

WARNINGS

For externaluse only.

DO NOT USE

on children under two years of age unless directed by a doctor.

WHEN USING

avoid contact withthe eyes.

ASK DOCTOR

irritation occurs-there is no improvement within 2 weeks for jock itch or within 4 weeks for athlete's foot and ringworm.

KEEP OUT OF REACH OF CHILDREN

lf swallowed,call poison control or seek medical help.

INDICATIONS AND USAGE

- Wash affected area well, rinse after 2 minutes. Dry thoroughly.
- Use twice daily (morning and night) or as directed by a doctor.
- Supervise children in the use of this product.
- For athlete's foot: Pay special attention to spaces between the toes; wear wellfitting, ventilated shoes, and change shoes and socks at least once daily.
- For athlete's foot and ringworm, use daily for 4 weeks, for jock itch, use dailyfor 2 weeks. lf condition persists longer, consult a doctor.
- This product is not effective on the scalp or nails.

OTHER SAFETY INFORMATION

store at room temperature and keep away from direct sunlight.

INACTIVE INGREDIENT

Sorbitol, Sucrose, Stearic Acid, Tallow, Cocamidopropyl Betaine, Propanediol,Glycerin, Sodium Laureth Sulfate, Water (Aqua), Lauric Acid, Sodium Hydroxide,Sodium Citrate, Charcoal Powder, Volcanic Ash, Melaleuca Alternifolia (Tea Tree)Leaf Oil, Aloe Barbadensis Leaf Extract, Butyrospermum Parkii (Shea) Butter,Mentha Arvensis Leaf Oil